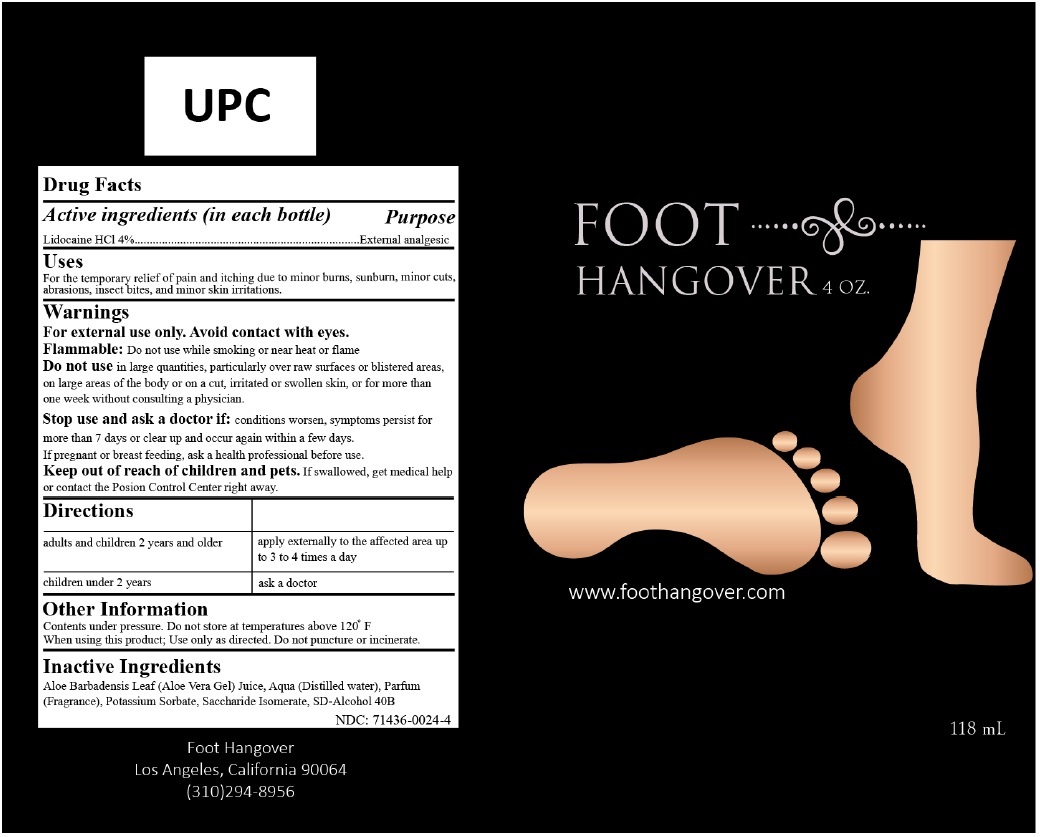 DRUG LABEL: FOOT HANGOVER
NDC: 71436-0024 | Form: LIQUID
Manufacturer: Ari Brands, Llc
Category: otc | Type: HUMAN OTC DRUG LABEL
Date: 20180131

ACTIVE INGREDIENTS: LIDOCAINE HYDROCHLORIDE 4 g/100 mL
INACTIVE INGREDIENTS: ALOE VERA LEAF; WATER; POTASSIUM SORBATE; SACCHARIDE ISOMERATE; ALCOHOL

FOOT HANGOVER

Active ingredients (in each bottle)

Lidocaine HCL 4%

Purpose

External analgesic

Uses

For the temporary relief of pain and itching due to minor burns, sunburn, minor cuts, abrasions, insect bites, and minor skin irritations.

Warnings

For external use only. Avoid contact with eyes.

Flammable: Do not use while smoking or near heat or flame.

Do not use in large quantities, particularly over raw surfaces or blistered areas, on large areas of the body or on a cut, irritated or swollen skin, or for more than one week without consulting a physician.

Stop use and ask a doctor if: conditions worsen, symptoms persist for more than 7 days or clear up and occur again within a few days.

If pregnant or breast feeding, ask a health professional before use.

Keep out of reach of children and pets. If swallowed, get medical help or contact the Poison Control Center right away.

Directions
adults and children 2 years and older | apply externally to the affected area up to 3 to 4 times a day
children under 2 years | ask a doctor

Other Information

Contents under pressure. Do not store at temperatures above 120° F

When using this product; Use only as directed. Do not puncture or incinerate.

Inactive Ingredients

Aloe Barbadensis Leaf (Aloe Vera Gel) Juice, Aqua (Distilled water), Parfum (Fragrance), Potassium Sorbate, Saccharide Isomerate, SD-Alcohol 40B

Foot Hangover

Los Angeles, California 90064

(310)294-8956